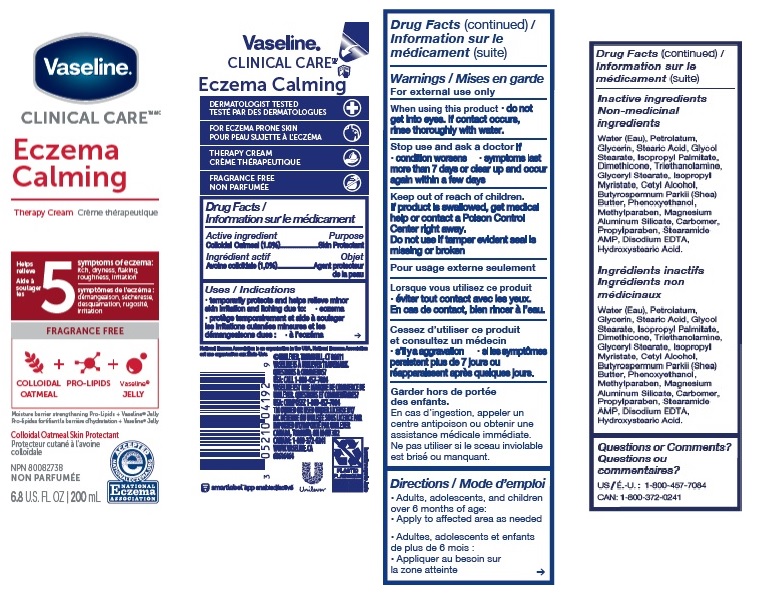 DRUG LABEL: Vaseline
NDC: 64942-1867 | Form: LOTION
Manufacturer: Conopco, Inc. d/b/a/ Unilever
Category: otc | Type: HUMAN OTC DRUG LABEL
Date: 20241107

ACTIVE INGREDIENTS: OATMEAL 1 g/100 mL
INACTIVE INGREDIENTS: WATER; GLYCERIN; STEARIC ACID; ISOPROPYL PALMITATE; GLYCOL STEARATE; DIMETHICONE; GLYCERYL MONOSTEARATE; PETROLATUM; CETYL ALCOHOL; PHENOXYETHANOL; METHYLPARABEN; CARBOMER INTERPOLYMER TYPE A (ALLYL SUCROSE CROSSLINKED); TROLAMINE; PROPYLPARABEN; STEARAMIDE AMP; EDETATE DISODIUM; MAGNESIUM ALUMINUM SILICATE; SHEA BUTTER; ISOPROPYL MYRISTATE; 12-HYDROXYSTEARIC ACID

Vaseline Clinical Care Eczema Calming Therapy Cream

Description

VASELINE CLINICAL CARE ECZEMA CALMING THERAPY CREAM - (colloidal oatmeal) lotion

Drug Facts

Active ingredient
Colloidal Oatmeal (1%)

Purpose

Skin Protectant

Uses

temporarily protects and helps relieve minor skin irritation and itching due to: eczema

Warnings

For external use only
When using this product do not get into eyes. If contact occurs, rinse thoroughly with water.
Stop use and ask a doctor if

- condition worsens
- symptoms last more than 7 days or clear up and occur again within a few days

Keep out of reach of children. If product is swallowed, get medical help or contact a Poison Control Center right away.

Directions

Adults, adolescents, and children over 6 months of age: Apply to affected area as needed

Inactive ingredients

Water (Eau), Petrolatum, Glycerin, Stearic Acid, Glycol Stearate, Isopropyl Palmitate, Dimethicone, Triethanolamine, Glyceryl Stearate, Isopropyl Myristate, Cetyl Alcohol, Butyrospermum Parkii (Shea) Butter, Phenoxyethanol, Methylparaben, Magnesium Aluminum Silicate, Carbomer, Propylparaben, Stearamide AMP, Disodium EDTA, Hydroxystearic Acid.

Questions or comments?

1-800-457-7084